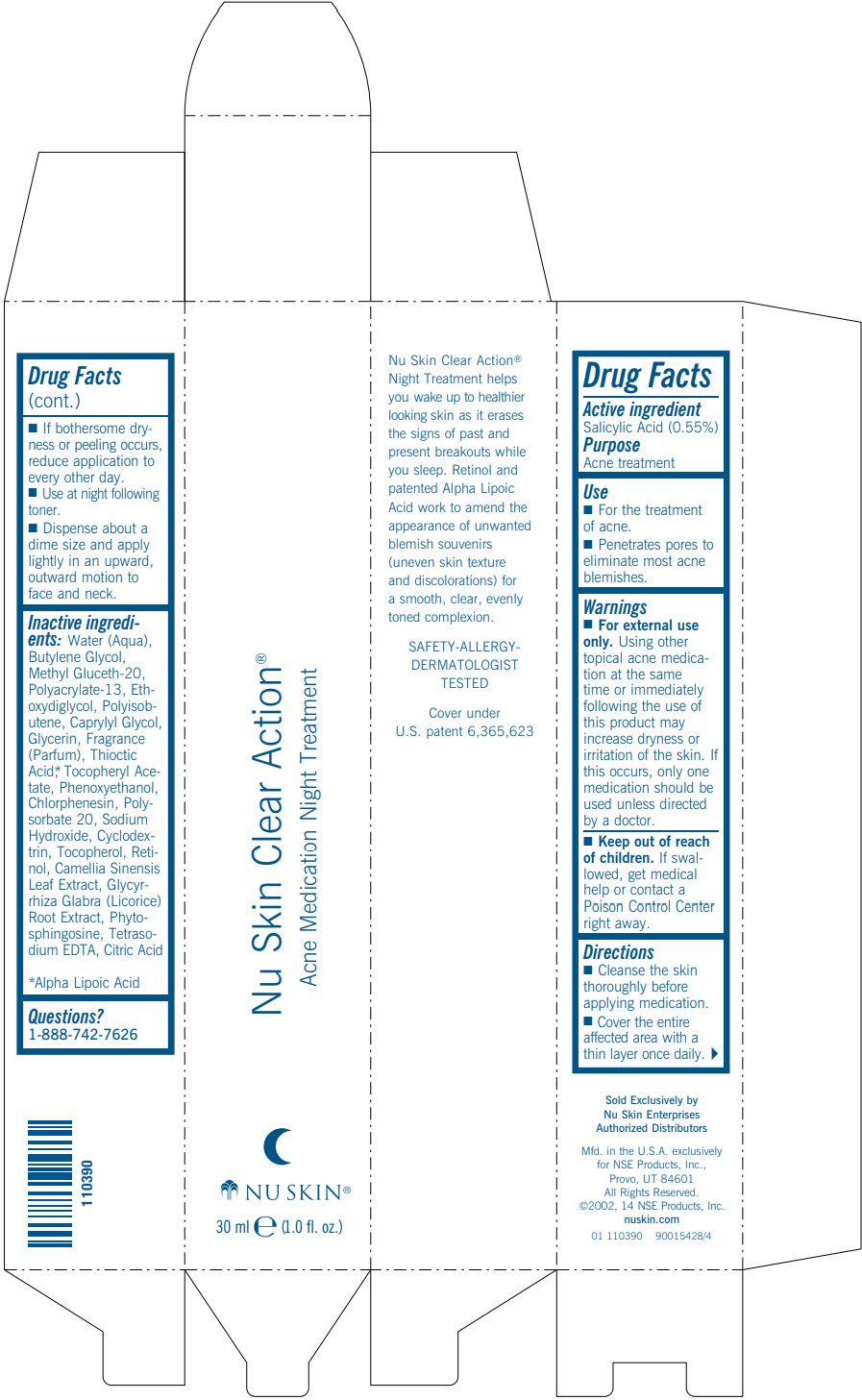 DRUG LABEL: Nu Skin Clear Action Acne Medication Night Treatment
NDC: 62839-4731 | Form: GEL
Manufacturer: NSE Products, Inc
Category: otc | Type: HUMAN OTC DRUG LABEL
Date: 20250106

ACTIVE INGREDIENTS: Salicylic Acid 5.5 g/1000 mL
INACTIVE INGREDIENTS: Water; Butylene Glycol; Methyl Gluceth-20; Diethylene Glycol Monoethyl Ether; Caprylyl Glycol; Glycerin; ALPHA LIPOIC ACID; Phenoxyethanol; Chlorphenesin; Polysorbate 20; Sodium Hydroxide; Tocopherol; Retinol; GREEN TEA LEAF; Licorice; Phytosphingosine; Edetate Sodium; Citric Acid Monohydrate

Nu Skin Clear Action® Acne Medication Night Treatment

Drug Facts

Active ingredient

Salicylic Acid (0.55%)

Purpose

Acne treatment

Use

- For the treatment of acne.
- Penetrates pores to eliminate most acne blemishes.

Warnings

- For external use only. Using other topical acne medication at the same time or immediately following the use of this product may increase dryness or irritation of the skin. If this occurs, only one medication should be used unless directed by a doctor.

- Keep out of reach of children. If swallowed, get medical help or contact a Poison Control Center right away.

Directions

- Cleanse the skin thoroughly before applying medication.
- Cover the entire affected area with a thin layer once daily.
- If bothersome dryness or peeling occurs, reduce application to every other day.
- Use at night following toner.
- Dispense about a dime size and apply lightly in an upward, outward motion to face and neck.

Inactive ingredients

Water (Aqua), Butylene Glycol, Methyl Gluceth-20, Polyacrylate-13, Ethoxydiglycol, Polyisobutene, Caprylyl Glycol, Glycerin, Fragrance (Parfum), Thioctic Acid, [Alpha Lipoic Acid] Tocopheryl Acetate, Phenoxyethanol, Chlorphenesin, Polysorbate 20, Sodium Hydroxide, Cyclodextrin, Tocopherol, Retinol, Camellia Sinensis Leaf Extract, Glycyrrhiza Glabra (Licorice) Root Extract, Phytosphingosine, Tetrasodium EDTA, Citric Acid

Questions?

1-888-742-7626

PRINCIPAL DISPLAY PANEL - 30 ml Tube Carton

Nu Skin Clear Action®
Acne Medication Night Treatment

NU SKIN®

30 ml e (1.0 fl. oz.)